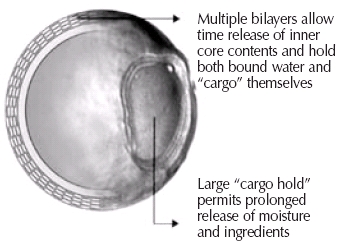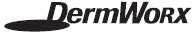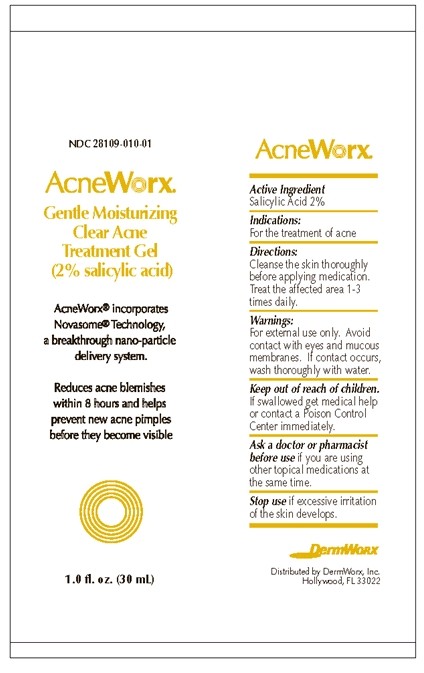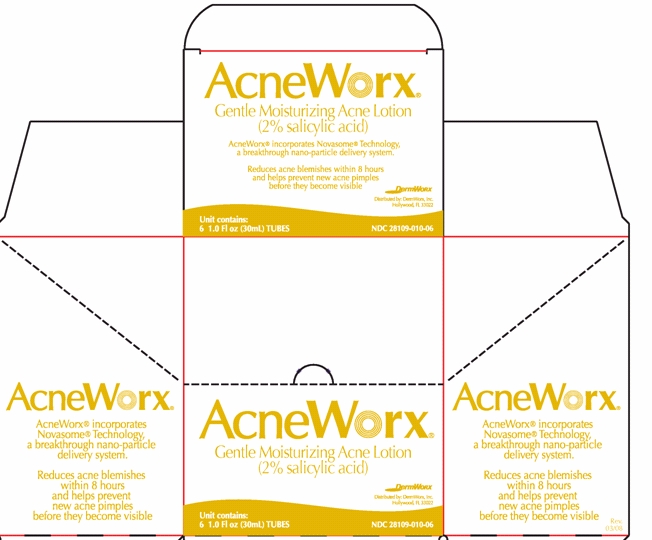 DRUG LABEL: AcneWorx
NDC: 28109-010 | Form: GEL
Manufacturer: DermWorx Incorporated
Category: otc | Type: HUMAN OTC DRUG LABEL
Date: 20100218

ACTIVE INGREDIENTS: SALICYLIC ACID 0.6 g/30 mL

AcneWorx® Gentle Moisturizing Clear Acne Treatment Gel
(2% Salicylic Acid)

Active ingredient

Salicylic Acid 2%

Purpose

Treatment of acne

Uses

For the treatment of acne

Warnings

For external use only. Avoid contact with eyes and mucous membranes. If contact occurs, wash thoroughly with water.

Ask a doctor or pharmacist

before use if you are using other topical medications at the same time.

Stop use

if excessive irritation of the skin develops.

Keep out of reach of children.

If swallowed get medical help or contact a Poison Control Center immediately.

Directions

Cleanse the skin thoroughly before applying medication. Cover the affected area with a thin layer 1-3 times daily.

Inactive ingredients

Water, Diisopropyl Adipate, Cyclomethicone, Glyceryl Stearate, Glyceryl Dilaurate, Glycerin, Ethoxydiglycol, Ethylhexyl Palmitate, L-Arginine, Stearoxymethicone/Dimethicone Copolymer, Cetearyl Alcohol, Cetyl Alcohol, PEG-150 Stearate, Polysorbate 80, Ethylene/Acrylic Acid Copolymer, Glycine Soja (soybean) Sterol, Tocopheryl Acetate, Phenoxyethanol, Cetearyl Glucoside, Xanthan Gum, Methylparaben, Disodium EDTA, Superoxide Dismutase, Citric Acid.

Patient Information

AcneWorx® is a maximum strength acne treatment that clears acne blemishes fast and helps prevent new breakouts before they become visible without the irritation caused by similar solvent-based formulations. AcneWorx® is a nano-based formulation utilizing Novasome® technology, a proprietary microsphere technology containing an effective acne-fighting medicine that penetrates pores to eliminate most acne blemishes.

Active Ingredient

Salicylic Acid 2%

Inactive Ingredients

Water, Diisopropyl Adipate, Cyclomethicone, Glyceryl Stearate, Glyceryl Dilaurate, Glycerin, Ethoxydiglycol, Ethylhexyl Palmitate, L-Arginine, Stearoxymethicone/Dimethicone Copolymer, Cetearyl Alcohol, Cetyl Alcohol, PEG-150 Stearate, Polysorbate 80, Ethylene/Acrylic Acid Copolymer, Glycine Soja (soybean) Sterol, Tocopheryl Acetate, Phenoxyethanol, Cetearyl Glucoside, Xanthan Gum, Methylparaben, Disodium EDTA, Superoxide Dismutase, Citric Acid

Indications

For the treatment of acne, especially, adult acne in men and women.

What is the Cause of Adult Acne?

Acne affects almost everyone, with more than 90% of all adolescents experiencing some form of acne and nearly 50% of all adult women and 25% of all adult men facing this skin disorder. Acne is prevalent in both men and women and is present in all ethnic backgrounds making it one of the most widespread medical conditions in the world.

A common misnomer is that acne is only for teenagers and will simply disappear once puberty is over. In fact, recent statistics reported by the American Dermatology Association suggest that the median age for patients being treated for acne has actually increased from approximately 20.5 to 26.5 years of age. More than 17 million adults in the U.S. are diagnosed with acne with over 50% of adult women and 25% of adult men having this skin disease.

So if you're one of many men or a woman with adult acne, you may be asking yourself what are the causes of acne.

Etiology (Causes) of Adult Acne

The underlying factors responsible for teenage acne are the same as those for adult acne:

1. Hormones

For the majority of acne sufferers puberty marks the onset of trouble, this is the time when the body begins to produce hormones called androgens. Testosterone in the skin can be metabolized to dihyrotestosterone, which causes the sebaceous glands to enlarge and increase sebum production. In acne sufferers, the sebaceous glands over-respond to androgens, sometimes well into adulthood. Androgens may also contribute to acne flare-ups associated with the menstrual cycle and, on occasion, pregnancy.

2. Over secretion of Sebaceous Glands

When the sebaceous gland is stimulated by dihydrotestosterone it produces extra sebum. Under normal circumstances sebum moves up the follicle toward the surface, the sebum mixes with normal skin bacteria and dead skin cells that have been shed from the lining of the follicle and removes them to the skin surface. While this process is normal, the presence of extra sebum in the follicle increases the chances of clogging and resultant acne.

3. Clogged Pores

Normally, dead cells within the follicle shed gradually and are expelled onto the skin's surface. In individuals with over-active sebaceous glands, these cells are shed more rapidly and mix with the surplus of sebum. The dead skin cells form a plug in the follicle causing either a blackhead or whitehead.

4. Bacteria

The bacterium, Propionibacterium acnes (P. acnes), is normally present in all skin types and is part of the skin's natural sebum maintenance system. Once a follicle is plugged the excess sebum supplies a rich environment for the P. acnes bacteria to multiply rapidly. This microenvironment creates the chemical reaction known as inflammation in the follicle and surrounding skin.

5. Local Inflammation

When your body encounters unwanted bacteria, it sends white blood cells to attack the “intruders”. This process is called chemotaxis and results in the inflammatory response, which causes pimples to become red, swollen, and painful. The inflammatory response is different for everyone, but studies have shown that it is especially strong in adult women. Thus, causing many adult women to experience particularly painful acne pimples.

Treatment of Adult Acne

In adult acne it is especially important to limit the number of pimples since dermatologists have known for many years that adult acne is more likely to leave permanent physical scars. The increase prevalence of scarring or pox marks is due to the fact that as the skin ages and loses collagen. It is much harder for the skin to repair itself after tissue damage that is caused by inflammation and enlarged pores associated with acne.

The standard treatments for adult acne are similar to those employed for adolescent acne, mainly topical products. These products often dry not only “pimples” but also the skin around them.

Salicylic acid is a widely used and well established ingredient in the pharmaceutical and healthcare areas. It has been used extensively in dermatological formulations as an exfoliate, anti-acne, anti-wart, anti-psoriatic and anti-aging agent.

The Food and Drug Administration Advisory Panel reviewed a number of well-controlled clinical studies for the treatment of acne and adult acne. In a primary 12-week acne study of 180 subjects, good to excellent results for total lesions were obtained by 40 percent of the subjects using 2% salicylic acid.

Similarly, the placebo showed improvement in only 5% of the subjects while only 2% of the subjects using benzoyl peroxide showed improvement. Salicylic acid was particularly effective in treating inflammatory lesions (papules and pustules) where 80% of the subjects had good or excellent results compared to 11% for the vehicle and 15% for benzoyl peroxide. Salicylic acid has clearly shown its superiority over benzoyl peroxide in the treatment of acne.

Despite its wide use, salicylic acid has some basic formulation limitations, which do not allow its optimal properties to be achieved. The very low aqueous solubility of salicylic acid is a major obstacle in attaining significantly improved formulations and, hence, efficacy within a short time frame. In order to overcome the solubility issues, current marketed products have used various sol-vents (i.e. acetone, alcohol, etc.) to increase the solubility. However, these organic solvents are also skin irritants to the surrounding healthy skin and act as drying agents on the skin. AcneWoRx® does not contain any organic solvents.

The therapeutic effectiveness of salicylic acid depends upon the presence of moisture. Therefore, salicylic acid is usually incorporated into vehicles that occlude the area and promote hydration causing maceration of the skin. AcneWoRx® incorporates a novel, patented, nanoparticle proprietary process in its formulation. Formulations with nanoparticles containing salicylic acid provide greater penetration of lesions without an increased potential for irritation from the formulation.

The microvesicle process significantly increases this compound’s aqueous solubility, penetrability and stability. Novasome® technology utilizes proprietary organized lipid structures, lipid vesicle encapsulation technologies, cellulose structures, and micellar nanoparticles. This technology pro-vides for a nanoparticle in an aqueous transport system. Because the system is aqueous, irritating organic solvents such as ether, acetone, alcohol and witch hazel that are currently used in other products containing salicylic acid are eliminated without sacrificing efficacy relating to concentration.

The Patented Microvesicle

The microvesicle contains 3 moisture compartments: water outside of vesicle, water inside the core of the vesicle, and osmotically bound water in between the layers of the vesicle

Warnings

For external use only.

Ask a doctor or pharmacist before use if you are using other topical acne medications at the same time or immediately following the use of this product. This product may result in increased dryness or irritation of the skin. If this occurs, only one medication should be used unless directed by a doctor.

When using this product avoid contact with eyes and mucous membranes. If contact occurs, flush thoroughly with water.

Keep out of reach of children.

If swallowed get medical help or contact a Poison Control Center immediately.

Cautions:

Discontinue use if excessive irritation of the skin develops.

Directions:

Cleanse the skin thoroughly before applying medication. Cover the entire affected area with a thin layer 1-3 times daily. Because excessive drying of the skin may occur, start with one application daily, then gradually increase to two or three times daily if needed or as directed by a doctor. If bothersome dryness or peeling occurs, reduce application to once a day or every other day.

How Supplied:

1.0 fl oz (30 mL) Tube

NDC 28109-010-01

Distributed by DermWorx, Inc.

Hollywood, FL 33022

Principal Display Panel - Tube Label

28109-010-01
AcneWorx®
Gentle Moisturizing
Clear Acne
Treatment Gel
(2% Salicylic Acid)

AcneWorx® incorporates

Novasome® Technology,

a breakthrough nano-particle

delivery system.

Reduces acne blemishes

within 8 hours

and helps prevent

new acne pimples

before they become visible

1.0 FL oz (30 mL)

Tube Label

Principal Display Panel - Outer Carton Label

AcneWorx®
Gentle Moisturizing
Clear Acne
Treatment Gel
(2% Salicylic Acid)

Unit contains:

6 1.0 fl oz (30mL) TUBES

28109-010-06

Outer Carton Label